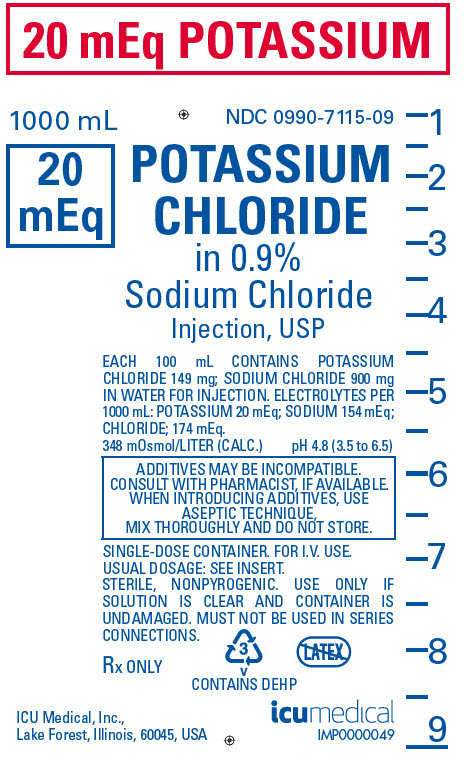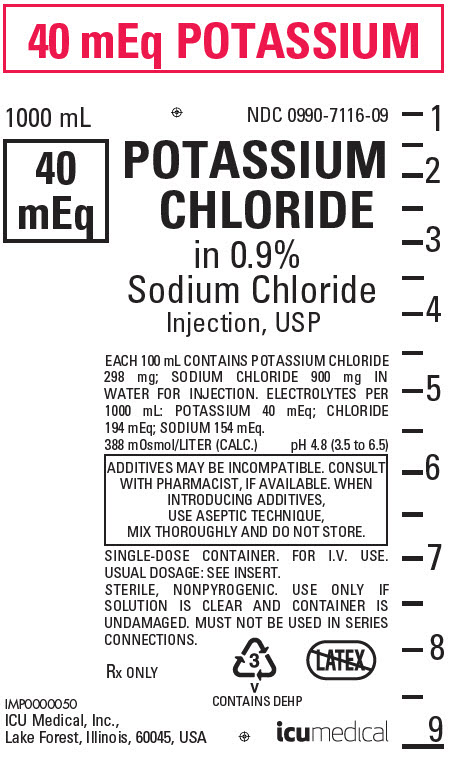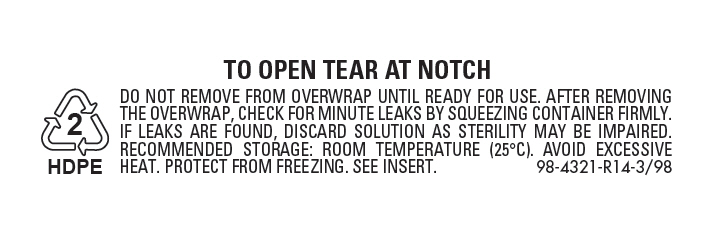 DRUG LABEL: Potassium Chloride in Sodium Chloride
NDC: 0990-7115 | Form: INJECTION, SOLUTION
Manufacturer: ICU Medical Inc.
Category: prescription | Type: HUMAN PRESCRIPTION DRUG LABEL
Date: 20251102

ACTIVE INGREDIENTS: SODIUM CHLORIDE 9 g/1000 mL; POTASSIUM CHLORIDE 1.49 g/1000 mL
INACTIVE INGREDIENTS: WATER

INTRAVENOUS SOLUTIONS
with POTASSIUM CHLORIDE

Potassium Chloride in 0.9% Sodium Chloride Injection, USP

Flexible Plastic Container
Rx only

DESCRIPTION

Intravenous solutions with potassium chloride (I.V. solutions with KCl) are sterile and nonpyrogenic solutions in water for injection. They are for administration by intravenous infusion only.

See Table for summary of content and characteristics of these solutions.

The solutions contain no bacteriostat, antimicrobial agent or added buffer and each is intended only for use as a single-dose injection. When smaller doses are required the unused portion should be discarded.

These solutions are parenteral fluid and/or electrolyte replenishers.

Potassium Chloride, USP is chemically designated KCl, a white granular powder freely soluble in water.

Sodium Chloride, USP is chemically designated NaCl, a white crystalline powder freely soluble in water.

Water for Injection, USP is chemically designated H20.

The flexible plastic container is fabricated from a specially formulated polyvinylchloride. Water can permeate from inside the container into the overwrap but not in amounts sufficient to affect the solution significantly. Solutions inside the plastic container also can leach out certain of its chemical components in very small amounts before the expiration period is attained. However, the safety of the plastic has been confirmed by tests in animals according to USP biological standards for plastic containers.

CLINICAL PHARMACOLOGY

When administered intravenously, these solutions provide a source of water and potassium chloride with 0.9% sodium chloride.

Intravenous solutions containing potassium chloride are particularly intended to provide needed potassium cation (K^+). Potassium is the chief cation of body cells (160 mEq/liter of intracellular water). It is found in low concentration in plasma and extracellular fluids (3.5 to 5.0 mEq/liter in a healthy adult). Potassium plays an important role in electrolyte balance. Normally about 80 to 90% of the potassium intake is excreted in the urine; the remainder in the stools and to a small extent, in the perspiration. The kidney does not conserve potassium well so that during fasting or in patients on a potassium-free diet, potassium loss from the body continues resulting in potassium depletion. A deficiency of either potassium or chloride will lead to a deficit of the other.

Sodium chloride in water dissociates to provide sodium (Na^+) and chloride (Cl¯) ions. Sodium (Na^+) is the principal cation of the extracellular fluid and plays a large part in the therapy of fluid and electrolyte disturbances. Chloride (Cl¯) has an integral role in buffering action when oxygen and carbon dioxide exchange occurs in the red blood cells. The distribution and excretion of sodium (Na^+) and chloride (Cl¯) are largely under the control of the kidney which maintains a balance between intake and output.

Water is an essential constituent of all body tissues and accounts for approximately 70% of total body weight. Average normal adult daily requirement ranges from two to three liters (1.0 to 1.5 liters each for insensible water loss by perspiration and urine production).

Water balance is maintained by various regulatory mechanisms. Water distribution depends primarily on the concentration of electrolytes in the body compartments and sodium (Na^+) plays a major role in maintaining physiologic equilibrium.

INDICATIONS AND USAGE

These solutions are indicated in patients requiring parenteral administration of potassium chloride and sodium chloride.

CONTRAINDICATIONS

Solutions containing potassium chloride are contraindicated in diseases where high potassium levels may be encountered.

WARNINGS

Solutions which contain potassium ions should be used with great care, if at all, in patients with hyperkalemia, severe renal failure and in conditions in which potassium retention is present.

To avoid potassium intoxication, do not infuse these solutions rapidly. In patients with severe renal insufficiency or adrenal insufficiency, administration of potassium chloride may cause potassium intoxication.

Solutions containing sodium ions should be used with great care, if at all, in patients with congestive heart failure, severe renal insufficiency and in clinical states in which there exists edema with sodium retention.

In patients with diminished renal function, administration of solutions containing sodium or potassium ions may result in sodium or potassium retention.

The intravenous administration of these solutions can cause fluid and/or solute overloading resulting in dilution of serum electrolyte concentrations, overhydration, congested states or pulmonary edema.

The risk of dilutional states is inversely proportional to the electrolyte concentration of administered parenteral solutions. The risk of solute overload causing congested states with peripheral and pulmonary edema is directly proportional to the electrolyte concentrations of such solutions.

PRECAUTIONS

Clinical evaluation and periodic laboratory determinations are necessary to monitor changes in fluid balance, electrolyte concentrations and acid-base balance during prolonged parenteral therapy or whenever the condition of the patient warrants such evaluation.

Caution must be exercised in the administration of parenteral fluids, especially those containing sodium ions, to patients receiving corticosteroids or corticotropin.

Potassium replacement therapy should be guided primarily by serial electrocardiograms. Plasma potassium levels are not necessarily indicative of tissue potassium levels.

High plasma concentrations of potassium may cause death through cardiac depression, arrhythmias or arrest.

Potassium-containing solutions should be used with caution in the presence of cardiac disease, particularly in digitalized patients or in the presence of renal disease.

Care should be exercised to insure that the needle (or catheter) is well within the lumen of the vein and that extravasation does not occur.

Do not administer unless solution is clear and container is undamaged. Discard unused portion.

PREGNANCY

Pregnancy Category C: Animal reproduction studies have not been conducted with potassium chloride or sodium chloride. It is also not known whether potassium chloride or sodium chloride can cause fetal harm when administered to a pregnant woman or can affect reproduction capacity. Potassium chloride or sodium chloride should be given to a pregnant woman only if clearly needed.

Pediatric Use

The safety and effectiveness in the pediatric population are based on the similarity of the clinical conditions of the pediatric and adult populations. In neonates or very small infants the volume of fluid may affect fluid and electrolyte balance.

ADVERSE REACTIONS

Reactions which may occur because of the solutions or technique of administration include febrile response, infection at the site of injection, venous thrombosis or phlebitis extending from the site of injection, extravasation and hypervolemia.

If an adverse reaction does occur, discontinue the infusion, evaluate the patient, institute appropriate therapeutic countermeasures and save the remainder of the fluid for examination if deemed necessary.

Nausea, vomiting, abdominal pain and diarrhea have been reported with potassium therapy. The signs and symptoms of potassium intoxication include paresthesias of the extremities, flaccid paralysis, listlessness, mental confusion, weakness and heaviness of the legs, hypotension, cardiac arrhythmias, heart block, electrocardiographic abnormalities such as disappearance of P waves, spreading and slurring of the QRS complex with development of a biphasic curve and cardiac arrest.

Potassium-containing solutions are intrinsically irritating to tissues. Therefore, extreme care should be taken to avoid perivascular infiltration. Local tissue necrosis and subsequent sloughing may result if extravasation occurs. Chemical phlebitis and venospasm have also been reported.

Should perivascular infiltration occur, I.V. administration at that site should be discontinued at once. Local infiltration of the affected area with procaine hydrochloride, 1%, to which hyaluronidase may be added, will often reduce venospasm and dilute the potassium remaining in the tissues locally. Local application of heat may also be helpful.

OVERDOSAGE

In the event of potassium overdosage, discontinue the infusion immediately and institute intensive corrective therapy to reduce serum potassium levels. (See WARNINGS and PRECAUTIONS.)

DOSAGE AND ADMINISTRATION

These solutions should be administered only by intravenous infusion and as directed by the physician. The dose and rate of injection are dependent upon the age, weight and clinical condition of the patient. If the serum potassium level is greater than 2.5 mEq/liter, potassium should be given at a rate not to exceed 10 mEq/hour in a concentration less than 30 mEq/liter. Somewhat faster rates and greater concentrations (usually up to 40 mEq/liter) of potassium may be indicated in patients with more severe potassium deficiency. The total 24-hour dose should not generally exceed 200 mEq of potassium.

Drug Interactions

Additives may be incompatible. Consult with pharmacist, if available. When introducing additives, use aseptic technique, mix thoroughly and do not store.

Parenteral drug products should be inspected visually for particulate matter and discoloration prior to administration, whenever solution and container permit. (See PRECAUTIONS.)

INSTRUCTIONS FOR USE

To Open

Tear outer wrap at notch and remove solution container. If supplemental medication is desired, follow directions below before preparing for administration. Some opacity of the plastic due to moisture absorption during the sterilization process may be observed. This is normal and does not affect the solution quality or safety. The opacity will diminish gradually.

To Add Medication

1. Prepare additive port.
2. Using aseptic technique and an additive delivery needle of appropriate length, puncture resealable additive port at target area, inner diaphragm and inject. Withdraw needle after injecting medication.
3. The additive port may be protected by covering with an additive cap.
4. Mix container contents thoroughly.

Preparation for Administration

(Use aseptic technique)

1. Close flow control clamp of administration set.
2. Remove cover from outlet port at bottom of container.
3. Insert piercing pin of administration set into port with a twisting motion until the set is firmly seated. NOTE: See full directions on administration set carton.
4. Suspend container from hanger.
5. Squeeze and release drip chamber to establish proper fluid level in chamber.
6. Open flow control clamp and clear air from set. Close clamp.
7. Attach set to venipuncture device. If device is not indwelling, prime and make venipuncture.
8. Regulate rate of administration with flow control clamp.

WARNING: Do not use flexible container in series connections.

HOW SUPPLIED

Intravenous solutions with potassium chloride (I.V. solution with KCl) are supplied in single-dose flexible plastic containers. See Table:

Potassium Chloride in
0.9% Sodium Chloride
Inj., USP |  |  | COMPOSITION |  |  |  | Approx. Ionic Concentrations
 |  |  | (g/L) |  | Calculated |  | (mEq/L)
NDC No. | mEq Potassium | Size (mL) | Sodium Chloride | Potassium Chloride | Osmolarity; (mOsmol/L) | pH (range) | Sodium; (Na^+) | Potassium; (K^+) | Chloride; (Cl¯) | Approximate kcal/L
0409–7115–09 | 20 mEq | 1000 | 9 | 1.49 | 348 | 4.8 (3.5 to 6.5) | 154 | 20 | 174 | 0
0990–7115–09 | 20 mEq | 1000 | 9 | 1.49 | 348 | 4.8 (3.5 to 6.5) | 154 | 20 | 174 | 0
0409–7116–09 | 40 mEq | 1000 | 9 | 2.98 | 388 | 4.8 (3.5 to 6.5) | 154 | 40 | 194 | 0
0990–7116–09 | 40 mEq | 1000 | 9 | 2.98 | 388 | 4.8 (3.5 to 6.5) | 154 | 40 | 194 | 0

ICU Medical is transitioning NDC codes from the "0409" to a "0990" labeler code. Both NDC codes are expected to be in the market for a period of time.

Store at 20 to 25°C (68 to 77°F). [See USP Controlled Room Temperature.] Protect from freezing.

Revised: March, 2020

IFU0000168

ICU Medical, Inc., Lake Forest, Illinois, 60045, USA

PRINCIPAL DISPLAY PANEL - 20 mEq Bag Label

20 mEq POTASSIUM

1000 mL
NDC 0990-7115-09

20
mEq
POTASSIUM
CHLORIDE
in 0.9%
Sodium Chloride
Injection, USP

EACH 100 mL CONTAINS POTASSIUM
CHLORIDE 149 mg; SODIUM CHLORIDE 900 mg
IN WATER FOR INJECTION. ELECTROLYTES PER
1000 mL: POTASSIUM 20 mEq; SODIUM 154 mEq;
CHLORIDE; 174 mEq.
348 mOsmol/LITER (CALC.)
pH 4.8 (3.5 to 6.5)

ADDITIVES MAY BE INCOMPATIBLE.
CONSULT WITH PHARMACIST, IF AVAILABLE.
WHEN INTRODUCING ADDITIVES, USE
ASEPTIC TECHNIQUE,
MIX THOROUGHLY AND DO NOT STORE.

SINGLE-DOSE CONTAINER. FOR I.V. USE.
USUAL DOSAGE: SEE INSERT.
STERILE, NONPYROGENIC. USE ONLY IF
SOLUTION IS CLEAR AND CONTAINER IS
UNDAMAGED. MUST NOT BE USED IN SERIES
CONNECTIONS.

Rx ONLY

3
v
CONTAINS DEHP

ICU Medical, Inc.,
Lake Forest, Illinois, 60045, USA

icumedical
IMP0000049

PRINCIPAL DISPLAY PANEL - 40 mEq Bag Label

40 mEq POTASSIUM

1000 mL
NDC 0990-7116-09

40
mEq

POTASSIUM
CHLORIDE
in 0.9%
Sodium Chloride
Injection, USP

EACH 100 mL CONTAINS POTASSIUM CHLORIDE
298 mg; SODIUM CHLORIDE 900 mg IN
WATER FOR INJECTION. ELECTROLYTES PER
1000 mL: POTASSIUM 40 mEq; CHLORIDE
194 mEq; SODIUM 154 mEq.
388 mOsmol/LITER (CALC.)
pH 4.8 (3.5 to 6.5)

ADDITIVES MAY BE INCOMPATIBLE. CONSULT
WITH PHARMACIST, IF AVAILABLE. WHEN
INTRODUCING ADDITIVES,
USE ASEPTIC TECHNIQUE,
MIX THOROUGHLY AND DO NOT STORE.

SINGLE-DOSE CONTAINER. FOR I.V. USE.
USUAL DOSAGE: SEE INSERT.
STERILE, NONPYROGENIC. USE ONLY IF
SOLUTION IS CLEAR AND CONTAINER IS
UNDAMAGED. MUST NOT BE USED IN SERIES
CONNECTIONS.

Rx ONLY

3
v
CONTAINS DEHP

IMP0000050
ICU Medical, Inc.,
Lake Forest, Illinois, 60045, USA

icumedical

PRINCIPAL DISPLAY PANEL - 1000 mL Bag Pouch

TO OPEN TEAR AT NOTCH

DO NOT REMOVE FROM OVERWRAP UNTIL READY FOR USE. AFTER REMOVING
THE OVERWRAP, CHECK FOR MINUTE LEAKS BY SQUEEZING CONTAINER FIRMLY.
IF LEAKS ARE FOUND, DISCARD SOLUTION AS STERILITY MAY BE IMPAIRED.
RECOMMENDED STORAGE: ROOM TEMPERATURE (25°C). AVOID EXCESSIVE
HEAT. PROTECT FROM FREEZING. SEE INSERT.

98-4321-R14-3/98

2
HDPE